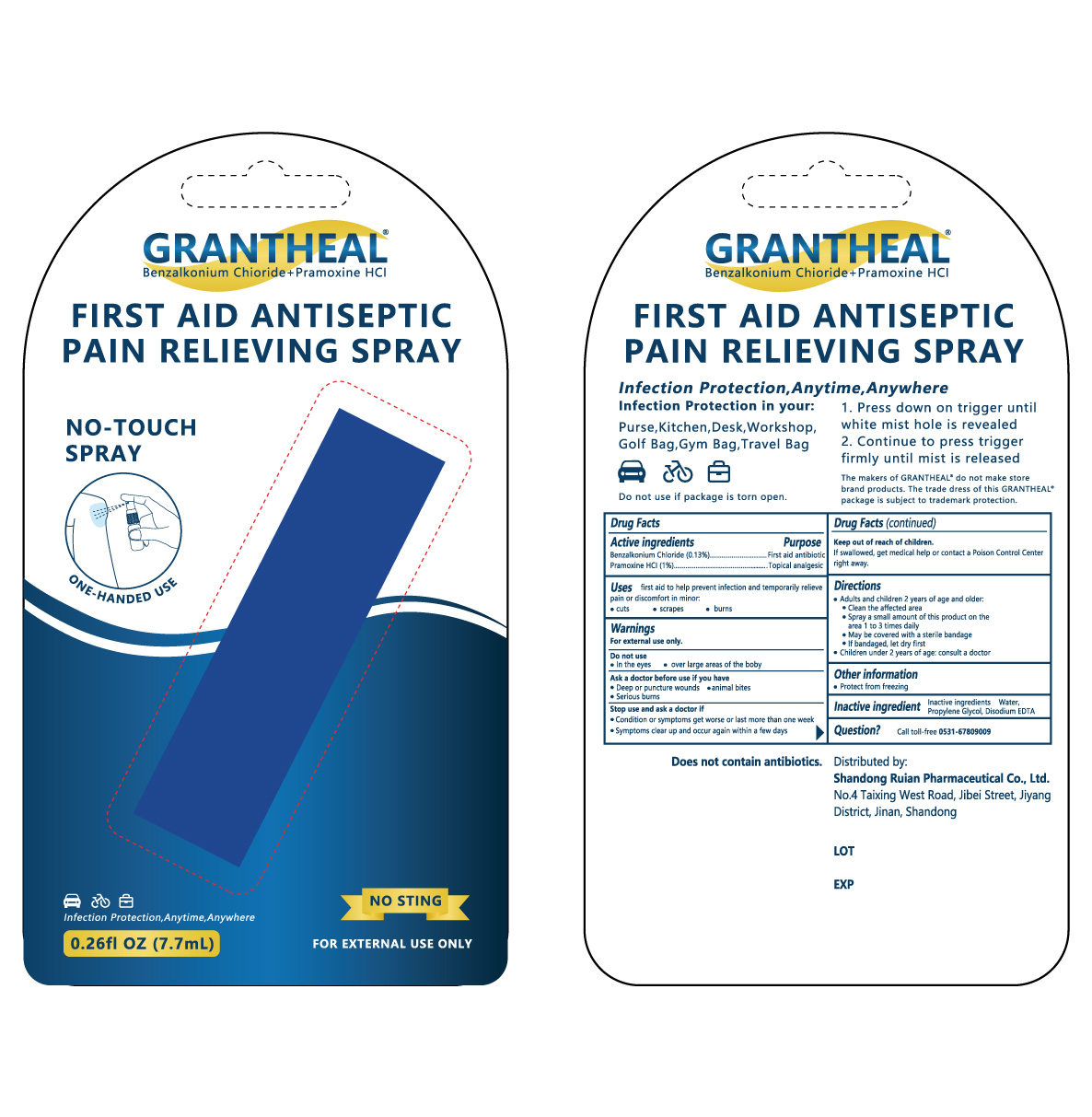 DRUG LABEL: First Aid Antiseptic Pain Relieving
NDC: 82199-610 | Form: SPRAY
Manufacturer: Shandong Ruian Pharmaceutical Co.,Ltd.
Category: otc | Type: HUMAN OTC DRUG LABEL
Date: 20211119

ACTIVE INGREDIENTS: BENZALKONIUM CHLORIDE 1.3 mg/1 mL; PRAMOXINE HYDROCHLORIDE 10 mg/1 mL
INACTIVE INGREDIENTS: WATER; EDETATE DISODIUM; PROPYLENE GLYCOL

ACTIVE INGREDIENT

BENZALKONIUM CHLORIDE;
PRAMOXINE HYDROCHLORIDE;

PURPOSE

First aid antibiotic
Topical analgesic

INDICATIONS AND USAGE

first aid to help prevent infection and for the temporary relief of pain or discomfort in minor:
• cuts
• scrapes
• burns

WARNINGS

For external use only

DO NOT USE

• in the eyes
• over large areas of the body

ASK DOCTOR

• deep or puncture wounds
• animal bites
• serious burns

STOP USE

• condition or symptoms get worse or last more than one week
• symptoms clear up and occur again within a few days
Keep out of reach of children.
If swallowed, get medical help or contact a Poison Control Centre right away.

DOSAGE AND ADMINISTRATION

• Adults and children 2 years of age and older:
• Clean the affected area
• Spray a small amount of this product on the area 1 to 3 times daily.
• May be covered with a sterile bandage
• If bandaged, let dry first
• Children under 2 years of age: consult a doctor

OTHER SAFETY INFORMATION

Store at Room Temperature

INACTIVE INGREDIENT

Water, Propylene Glycol, Edetate Disodium

KEEP OUT OF REACH OF CHILDREN

If swallowed, get medical help or contact a Poison Control Center right away.

PACKAGE LABEL

NDC: 82199-610-26 7.7ml in 1 Vial